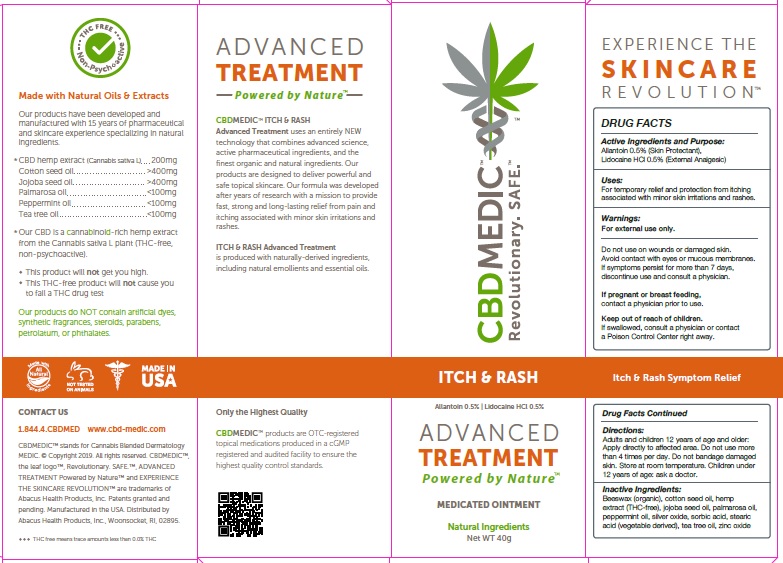 DRUG LABEL: CBDMEDIC Itch and Rash
NDC: 24909-731 | Form: OINTMENT
Manufacturer: AIDANCE SKINCARE & TOPICAL SOLUTIONS, LLC
Category: otc | Type: HUMAN OTC DRUG LABEL
Date: 20190306

ACTIVE INGREDIENTS: ALLANTOIN 5 mg/1 g; LIDOCAINE 5 mg/1 g
INACTIVE INGREDIENTS: WHITE WAX; COTTONSEED OIL; HEMP; JOJOBA OIL; PALMAROSA OIL; PEPPERMINT OIL; SILVER OXIDE; SORBIC ACID; STEARIC ACID; TEA TREE OIL; ZINC OXIDE

CBDMEDIC Itch and Rash

Active Ingredients and Purpose

Allantoin 0.5% (Skin Protectant),
Lidocaine HCl 0.5% (External Analgesic)

Uses

For temporary relief and protection from itching associated with minor skin irritations and rashes.

Warnings

For external use only. Do not use on wounds or damaged skin. Avoid contact with eyes or mucous membranes. If symptoms persist for more than 7 days, discontinue use and consult a physician.

KEEP OUT OF REACH OF CHILDREN

If pregnant or breast feeding, contact a physician prior to use.

Directions:

Adults and children 12 years of age and older: Apply directly to affected area. Do not use more than 4 times per day. Do not bandage damaged
skin. Store at room temperature. Children under 12 years of age: ask a doctor.

Inactive ingredients

Beeswax (organic), cotton seed oil, hemp extract (THC-free), jojoba seed oil, palmarosa oil, peppermint oil, silver oxide, sorbic acid, stearic
acid (vegetable derived), tea tree oil, zinc oxide